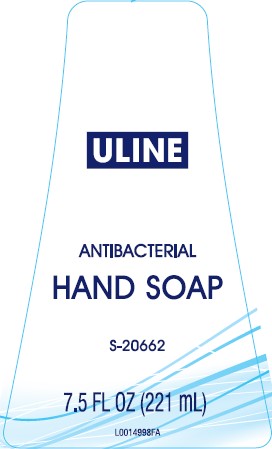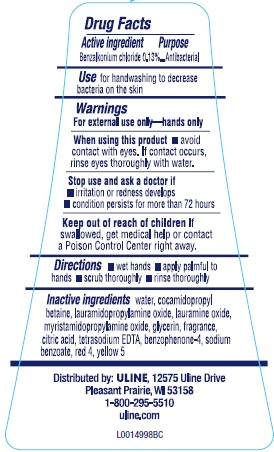 DRUG LABEL: Hand Wash
NDC: 69790-466 | Form: SOAP
Manufacturer: ULINE
Category: otc | Type: HUMAN OTC DRUG LABEL
Date: 20260217

ACTIVE INGREDIENTS: BENZALKONIUM CHLORIDE 1.3 mg/1 mL
INACTIVE INGREDIENTS: WATER; COCAMIDOPROPYL BETAINE; LAURAMIDOPROPYLAMINE OXIDE; LAURAMINE OXIDE; MYRISTAMIDOPROPYLAMINE OXIDE; GLYCERIN; CITRIC ACID MONOHYDRATE; EDETATE SODIUM; SULISOBENZONE; SODIUM BENZOATE; FD&C RED NO. 4; FD&C YELLOW NO. 5

Uline 466.001/466AB
Antibacterial Foaming Hand Wash

Active ingredient

Benzalkonium chloride 0.13%

purpose

Antibacterial

Use

for handwashing to decrease bacteria on the skin

warnings

For external use only: hands only

When using this product

- avoid contact with eyes. If contact occurs, rinse eyes thoroughly with water.

Stop use and ask a doctor if

- irritation or redness develops
- condition persists for more than 72 hours

Keep out of reach of children.

if swallowed, get medical help or contact a Poison Control Center right away.

Directions

- wet hands
- apply palmful to hands
- scrub thoroughly
- rinse thoroughly

Inactive ingredients

water, cocamidopropyl betaine, lauramidopropylamine oxide, lauramine oxide, myristamidopropylamine oxide, glycerin, fragrance, citric acid, tetrasodium EDTA, benzophenone-4, sodium benzoate, red 4, yellow 5

Adverse reactions

Distributed by: ULINE, 12575 Uline Drive

Pleasant Prairie, WI 53158

1-800-295-5510

uline.com

principal Display Panel

ULINE

ANTIBACTERIAL

HAND SOAP

S-20662

7.5 FL OZ (221 mL)